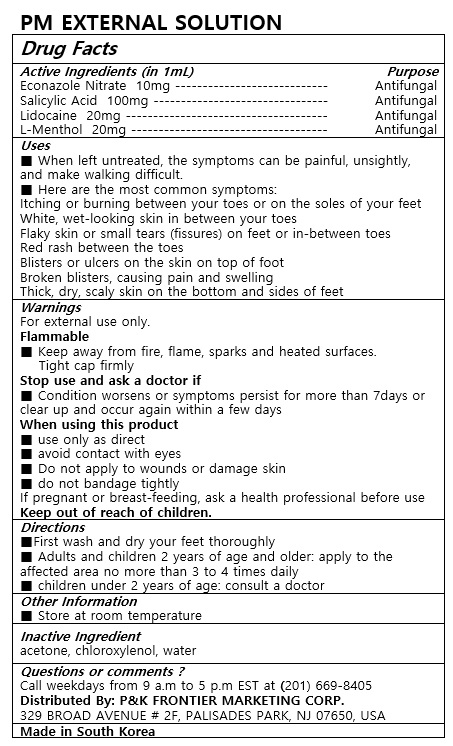 DRUG LABEL: PM EXTERNAL
NDC: 72689-0038 | Form: SOLUTION
Manufacturer: OASIS TRADING
Category: otc | Type: HUMAN OTC DRUG LABEL
Date: 20190319

ACTIVE INGREDIENTS: LEVOMENTHOL 20 mg/1 mL; SALICYLIC ACID 100 mg/1 mL; LIDOCAINE 20 mg/1 mL; ECONAZOLE NITRATE 10 mg/1 mL
INACTIVE INGREDIENTS: ACETONE; CHLOROXYLENOL

ACTIVE INGREDIENT

ECONAZOLE NITRATE, SALICYLIC ACID, LIDOCAINE, L-MENTHOL

PURPOSE

When left untreated, the symptoms can be painful, unsightly, and make walking difficult.
Here are the most common symptoms:
Itching or burning between your toes or on the soles of your feet
White, wet-looking skin in between your toes
Flaky skin or small tears (fissures) on feet or in-between toes
Red rash between the toes
Blisters or ulcers on the skin on top of foot
Broken blisters, causing pain and swelling
Thick, dry, scaly skin on the bottom and sides of feet

Keep out of reach of children

INDICATIONS AND USAGE

■First wash and dry your feet thoroughly
■ Adults and children 2 years of age and older: apply to the affected area no more than 3 to 4 times daily
■ children under 2 years of age: consult a doctor

WARNINGS

For external use olny.
Flammable
■ Keep away from fire, flame, sparks and heated surfaces.
Tight cap firmly
Stop use and ask a doctor if
■ Condition worsens or symptoms persist for more than 7days or clear up and occur again within a few days
When using this product
■ use olny as direct
■ avoid contact with eyes
■ Do not apply to wounds or damage skin
■ do not bandage tightly
If pregnant or breast-feeding, ask a health professional before use
keep out of reach of children.

INACTIVE INGREDIENT

acetone, chloroxylenol, water

DOSAGE AND ADMINISTRATION

For external use only